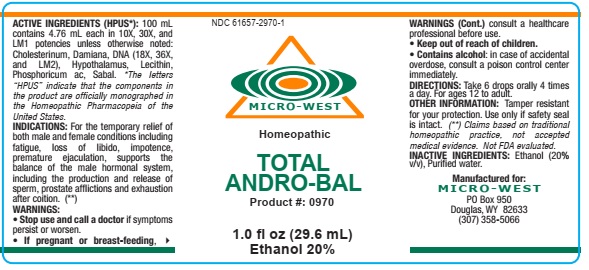 DRUG LABEL: TOTAL ANDRO BAL
NDC: 61657-2970 | Form: LIQUID
Manufacturer: White Manufacturing Inc. DBA Micro-West
Category: homeopathic | Type: HUMAN OTC DRUG LABEL
Date: 20210121

ACTIVE INGREDIENTS: CHOLESTEROL 10 [hp_X]/30 mL; TURNERA DIFFUSA LEAFY TWIG 10 [hp_X]/30 mL; HERRING SPERM DNA 10 [hp_X]/30 mL; BOS TAURUS HYPOTHALAMUS 18 [hp_X]/30 mL; EGG PHOSPHOLIPIDS 18 [hp_X]/30 mL; PHOSPHORIC ACID 18 [hp_X]/30 mL; SAW PALMETTO 18 [hp_X]/30 mL
INACTIVE INGREDIENTS: ALCOHOL; WATER

TOTAL ANDRO BAL

ACTIVE INGREDIENTS (HPUS*): 100 mL
contains 4.76 mL each in 10X, 30X, and
LM1 potencies unless otherwise noted:
Cholesterinum, Damiana, DNA (18X, 36X,
and LM2), Hypothalamus, Lecithin,
Phosphoricum ac, Sabal. *The letters
“HPUS” indicate that the components in
the product are officially monographed in
the Homeopathic Pharmacopeia of the
United States

INDICATIONS: For the temporary relief of
both male and female conditions including
fatigue, loss of libido, impotence,
premature ejaculation, supports the
balance of the male hormonal system,
including the production and release of
sperm, prostate afflictions and exhaustion
after coition. (**)

WARNINGS:
• Stop use and call a doctor if symptoms
persist or worsen.
• If pregnant or breast-feeding, consult a health care

professional before use.

• Keep out of reach of children.
• Contains alcohol: in case of accidental
overdose, consult a poison control center
immediately.

DOSAGE AND ADMINISTRATION

DIRECTIONS: Take 6 drops orally 4 times
a day. For ages 12 to adult.

OTHER INFORMATION: Tamper resistant
for your protection. Use only if safety seal
is intact. (**) Claims based on traditional
homeopathic practice, not accepted
medical evidence. Not FDA evaluated

INACTIVE INGREDIENTS: Ethanol (20%
v/v), Purified water.

QUESTIONS

Manufactured for:
MICRO-WEST
PO Box 950
Douglas, WY 82633
(307) 358-5066

PACKAGE LABEL

NDC 61657-2970-1

MICRO-WEST

Homeopathic
TOTAL
ANDRO-BAL
Product #: 0970

1.0 fl oz (29.6 mL)

Ethanol 20%

PURPOSE

For the temporary relief of
both male and female conditions including
fatigue, loss of libido, impotence,
premature ejaculation, supports the
balance of the male hormonal system,
including the production and release of
sperm, prostate afflictions and exhaustion
after coition. (**)